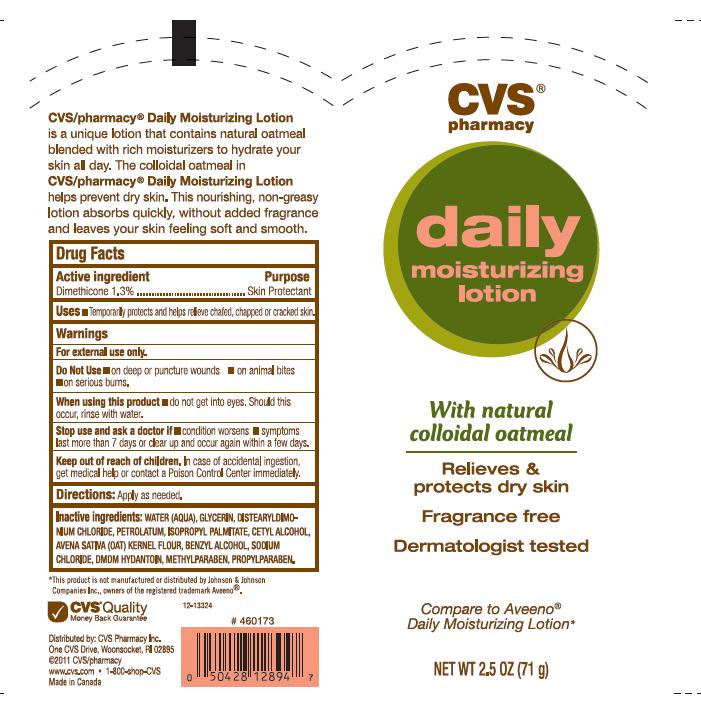 DRUG LABEL: DAILY MOISTURIZING
NDC: 59779-324 | Form: LOTION
Manufacturer: CVS PHARMACY
Category: otc | Type: HUMAN OTC DRUG LABEL
Date: 20111103

ACTIVE INGREDIENTS: DIMETHICONE 1.3 g/100 g
INACTIVE INGREDIENTS: WATER; GLYCERIN; DISTEARYLDIMONIUM CHLORIDE; PETROLATUM; ISOPROPYL PALMITATE; CETYL ALCOHOL; OATMEAL; BENZYL ALCOHOL; SODIUM CHLORIDE; DMDM HYDANTOIN; METHYLPARABEN; PROPYLPARABEN

DRUG FACTS

ACTIVE INGREDIENT

DIMETHICONE 1.3%

PURPOSE

SKIN PROTECTANT

USES

TEMPORARILY PROTECTS AND HELPS RELIEVE CHAFED, CHAPPED OR CRACKED SKIN.

WARNINGS

FOR EXTERNAL USE ONLY.

DO NOT USE

- ON DEEP PUNCTURE WOUNDS
- ON ANIMAL BITES
- ON SERIOUS BURNS

WHEN USING THIS PRODUCT

DO NOT GET INTO EYES. SHOULD THIS OCCUR, RINSE WITH WATER.

STOP USE AND ASK A DOCTOR IF

- CONDITION WORSENS
- SYMPTOMS LAST MORE THAN 7 DAYS OR CLEAR UP AND OCCUR AGAIN WITHIN A FEW DAYS.

KEEP OUT OF REACH OF CHILDREN

IN CASE OF ACCIDENTAL INGESTION, GET MEDICAL HELP OR CONTACT A POISON CONTROL CENTER IMMEDIATELY.

DIRECTIONS

APPLY AS NEEDED.

INACTIVE INGREDIENTS

WATER, GLYCERIN, DISTEARYLDIMONIUM CHLORIDE, PETROLATUM, ISOPROPYL MYRISTATE, CETYL ALCOHOL, AVENA SATIVA (OAT) KERNEL FLOUR, BENZYL ALCOHOL, SODIUM CHLORIDE, DMDM HYDANTOIN, METHYLPARABEN, PROPYLPARABEN.